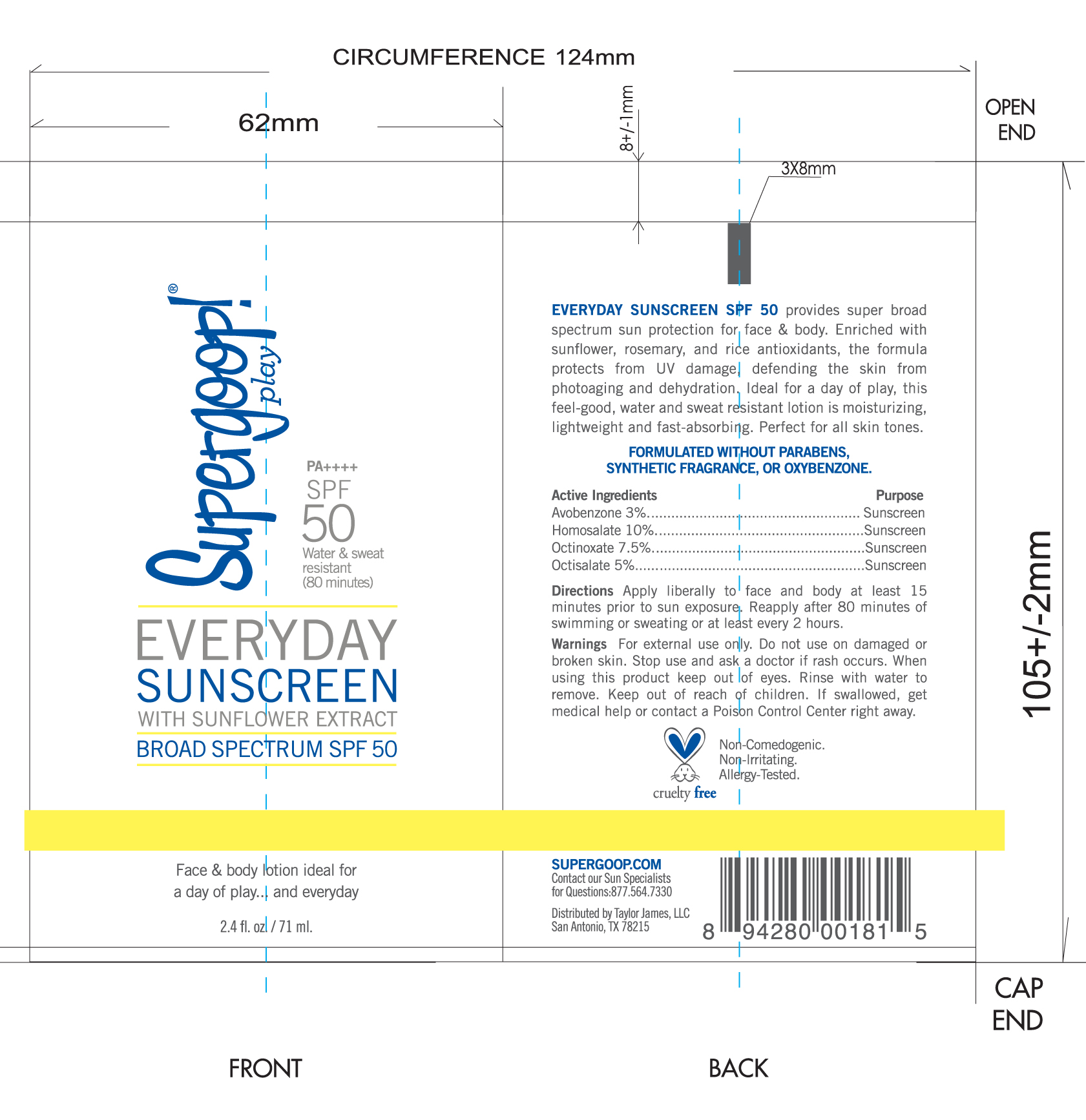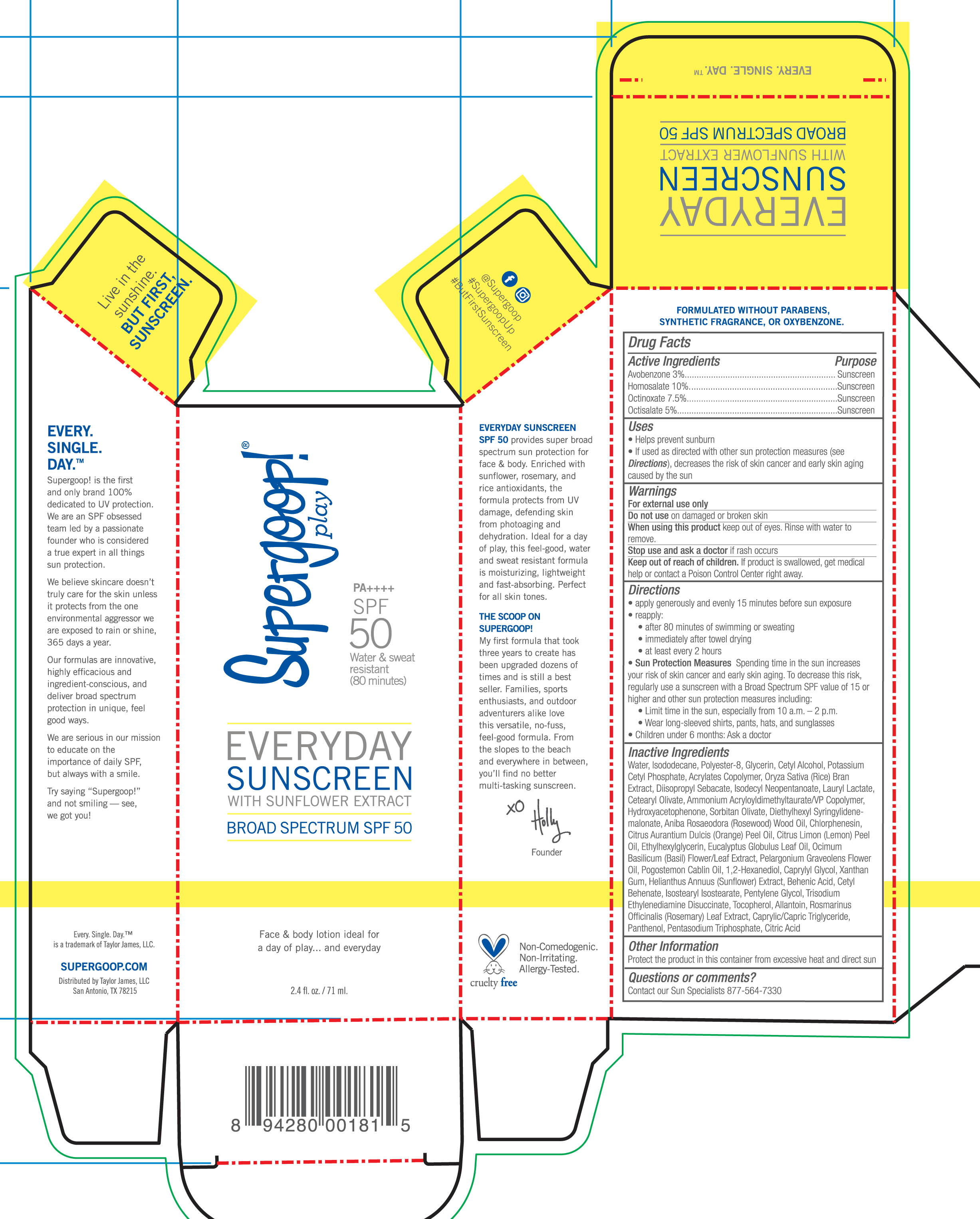 DRUG LABEL: EVERYDAY SUNSCREEN SPF 50 with Sunflower Extract
NDC: 75936-215 | Form: CREAM
Manufacturer: Taylor James
Category: otc | Type: HUMAN OTC DRUG LABEL
Date: 20190219

ACTIVE INGREDIENTS: OCTINOXATE 7.5 g/100 mL; OCTISALATE 5 g/100 mL; AVOBENZONE 3 g/100 mL; HOMOSALATE 10 g/100 mL
INACTIVE INGREDIENTS: WATER; GLYCERIN; CETYL ALCOHOL; ALLANTOIN; MEDIUM-CHAIN TRIGLYCERIDES; PANTHENOL; CITRIC ACID MONOHYDRATE; RICE BRAN; ISODECYL NEOPENTANOATE; LAURYL LACTATE; CETEARYL OLIVATE; SORBITAN OLIVATE; DIETHYLHEXYL SYRINGYLIDENEMALONATE; CHLORPHENESIN; EUCALYPTUS OIL; PELARGONIUM GRAVEOLENS FLOWER OIL; 1,2-HEXANEDIOL; CAPRYLYL GLYCOL; CETYL BEHENATE; ISOSTEARYL ISOSTEARATE; PENTYLENE GLYCOL; TRISODIUM ETHYLENEDIAMINE DISUCCINATE; TOCOPHEROL; SODIUM TRIPOLYPHOSPHATE ANHYDROUS; LEMON OIL; XANTHAN GUM; ROSEMARY; ISODODECANE; POLYESTER-8 (1400 MW, CYANODIPHENYLPROPENOYL CAPPED); POTASSIUM CETYL PHOSPHATE; DIISOPROPYL SEBACATE; HYDROXYACETOPHENONE; ROSEWOOD OIL; ORANGE OIL; ETHYLHEXYLGLYCERIN; PATCHOULI OIL; BEHENIC ACID

Everyday SPF 50 with Sunflower Extract

Active Ingredients Purpose

Avobenzone 3% Sunscreen

Homosalate 10% Sunscreen

Octinoxate 7.5% Sunscreen

Octisalate 5% Sunscree

Uses

- Helps Prevent Sunburn
- If used as directed with other sun protection measures (see Directions), decreases the risk of Skin cancer and early skin aging caused by the sun

Keep out of reach of children. If swallowed, get medical help or contact a Poison Control Center right away

Stop use and ask a doctor if rash occurs

Warnings

For External use only

Do not use on damaged or broken skin

When using this product, Keep out of eyes. Rinse with water to remove

Directions

Apply liberally 15 minutes before sun exposure

Reapply:

after 80 minutes of swimming or sweating
immediately after towel drying
at least every 2 hours
Sun Protection Measures. Spending time in the sun increases your risk of skin

cancer and early skin aging. To decrease this risk, regularly use a sunscreen
with broad spectrum SPF of 15 or higher and other sun protection measures
including:

limit time in the sun, especially from 10 a.m. - 2 p.m.
Wear Long-sleeved shirts, pants, hats, and sunglasses
Children under 6 months: Ask a doctor

Inactive Ingredients

Water, Isododecane, Polyester-8, Glycerin, Cetyl Alcohol, Potassium Cetyl Phosphate, Acrylates Copolymer, Oryza Sativa (Rice) Bran Extract, Diisopropyl Sebacate, Isodecyl Neopentanoate, Lauryl Lactate, Cetearyl Olivate, Ammonium Acryloyldimethyltaurate/VP Copolymer, Hydroxyacetophenone, Sorbitan Olivate, Diethylhexyl Syringylidenemalonate, Aniba Roseadora (Rosewood) Wood Oil, Chlorphenesin, Citrus Aurantium Dulcis (Orange) Peel Oil, Citrus Limon (Lemon) Peel Oil, Ethylhexylglycerin, Eucalyptus Globulus Leaf Oil, Ocimum Basilicum (Basil) Flower/leaf Extract, Pelargonium Graveolens Flower Oil, Pogostemon Cablin Oil, 1,2-Hexanediol, Caprylyl Glycol, Xanthan Gum, Helianthus Annuus (Sunflower) Extract, Behenix Acid, Cetyl Behenate, Isostearyl Isostearate, Pentylene Glycol, Trisodium Ethylenediamine Disuccinate, Tocopherol, Allantoin, Rosmarinus Officinalis (Rosemary) Leaf Extract, Caprylic/Capric Triglyceride, Panthenol, Pentasodium Triphosphate, Citric Acid

PACKAGE LABEL

Everyday Sunscreen with Sunflower Extract Broad Spectrum SPF 50

Water & Sweat resistant (80 minutes)

2.4 fl oz/ 71 ml